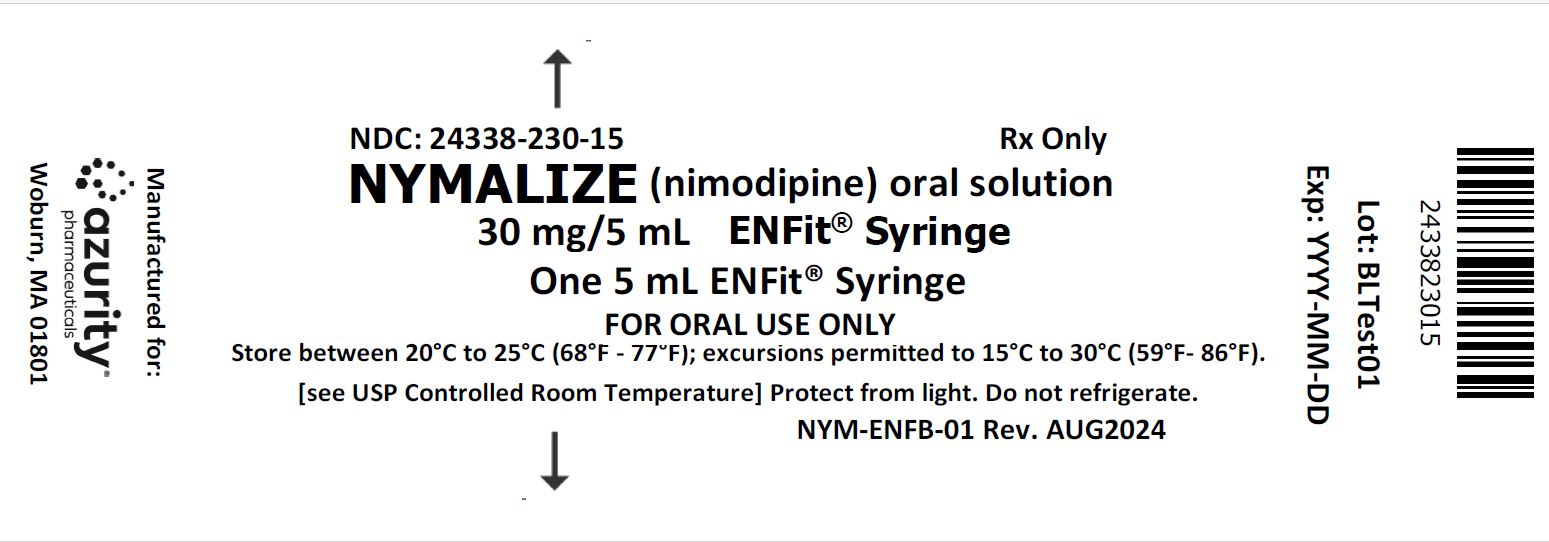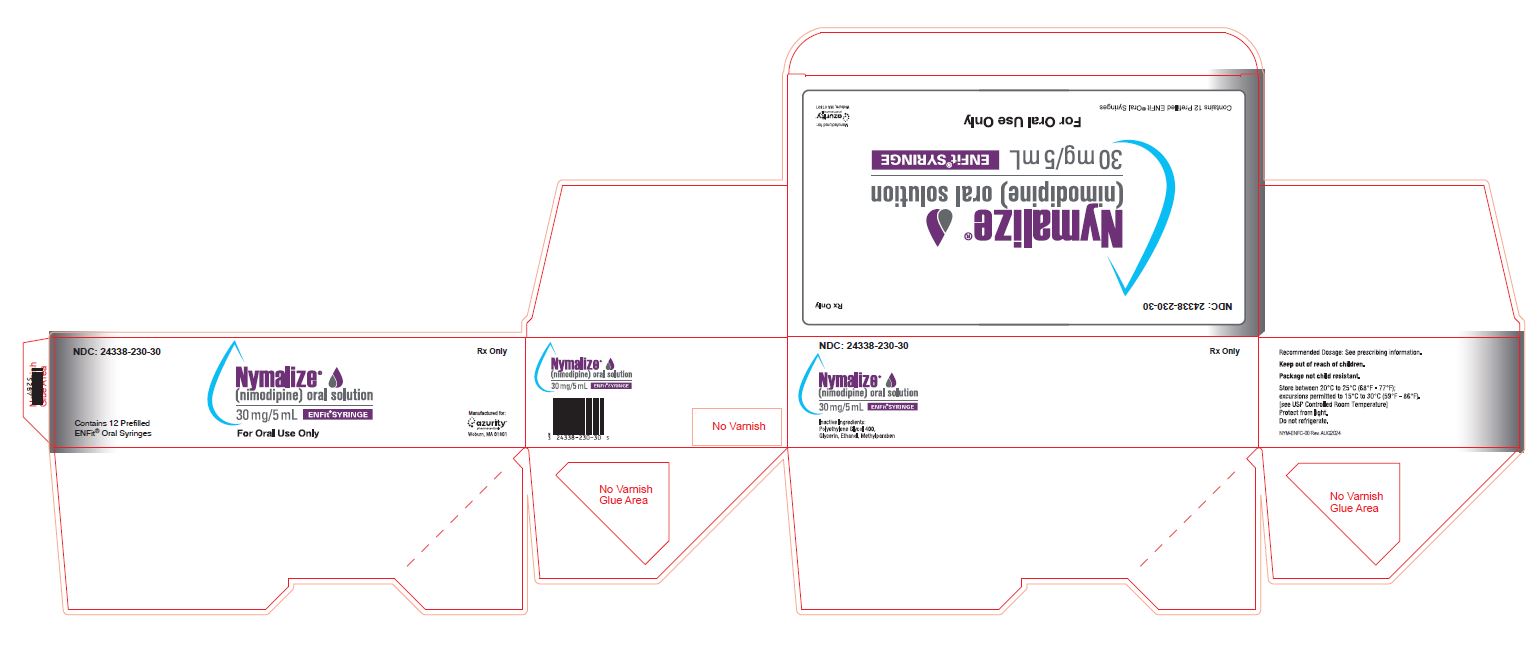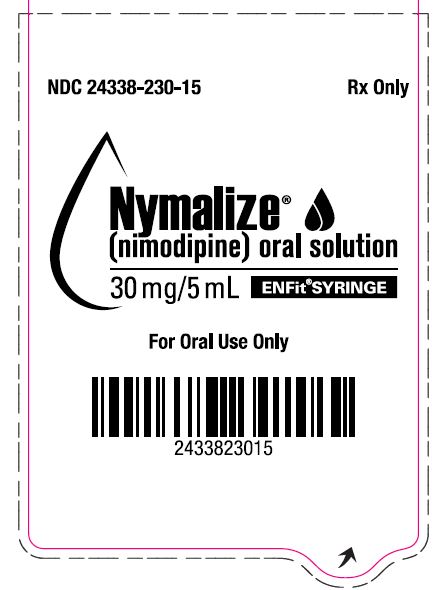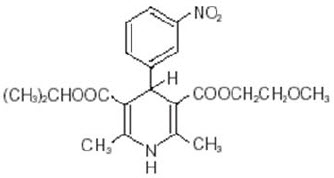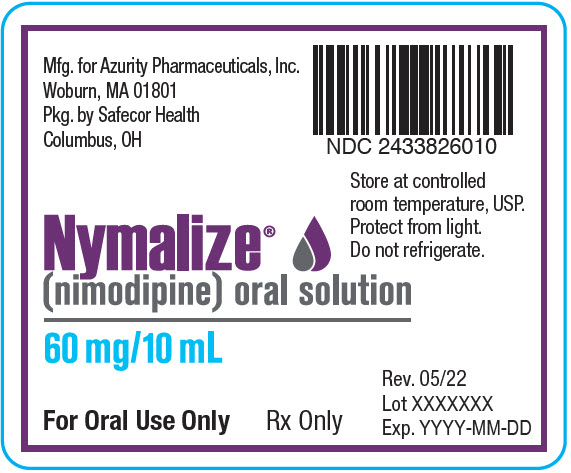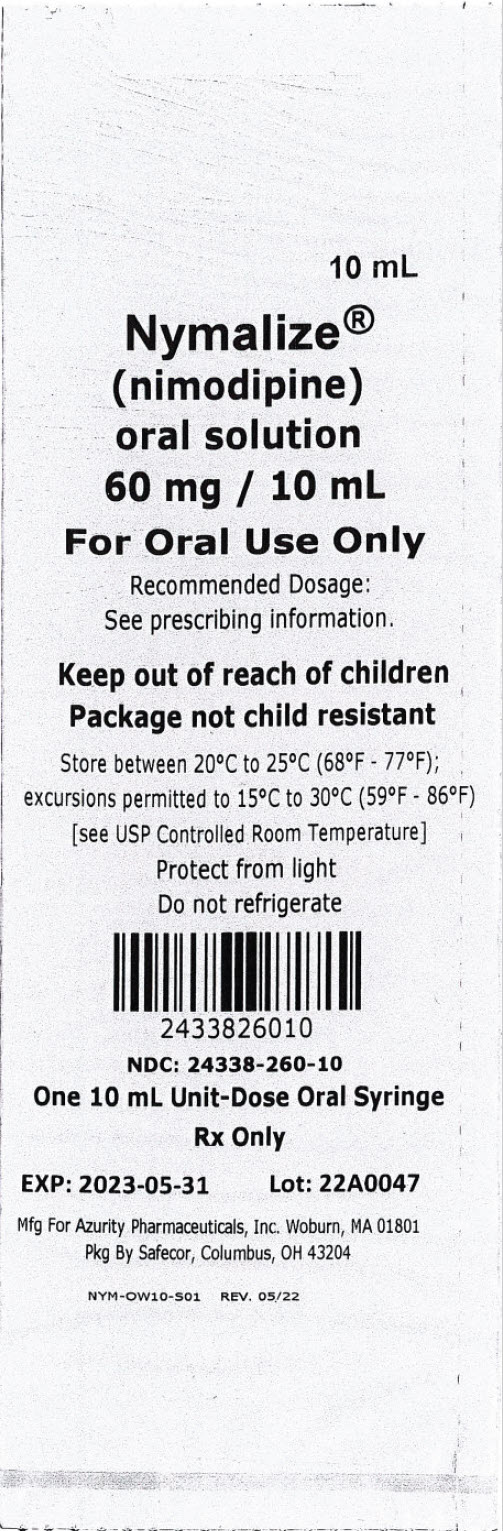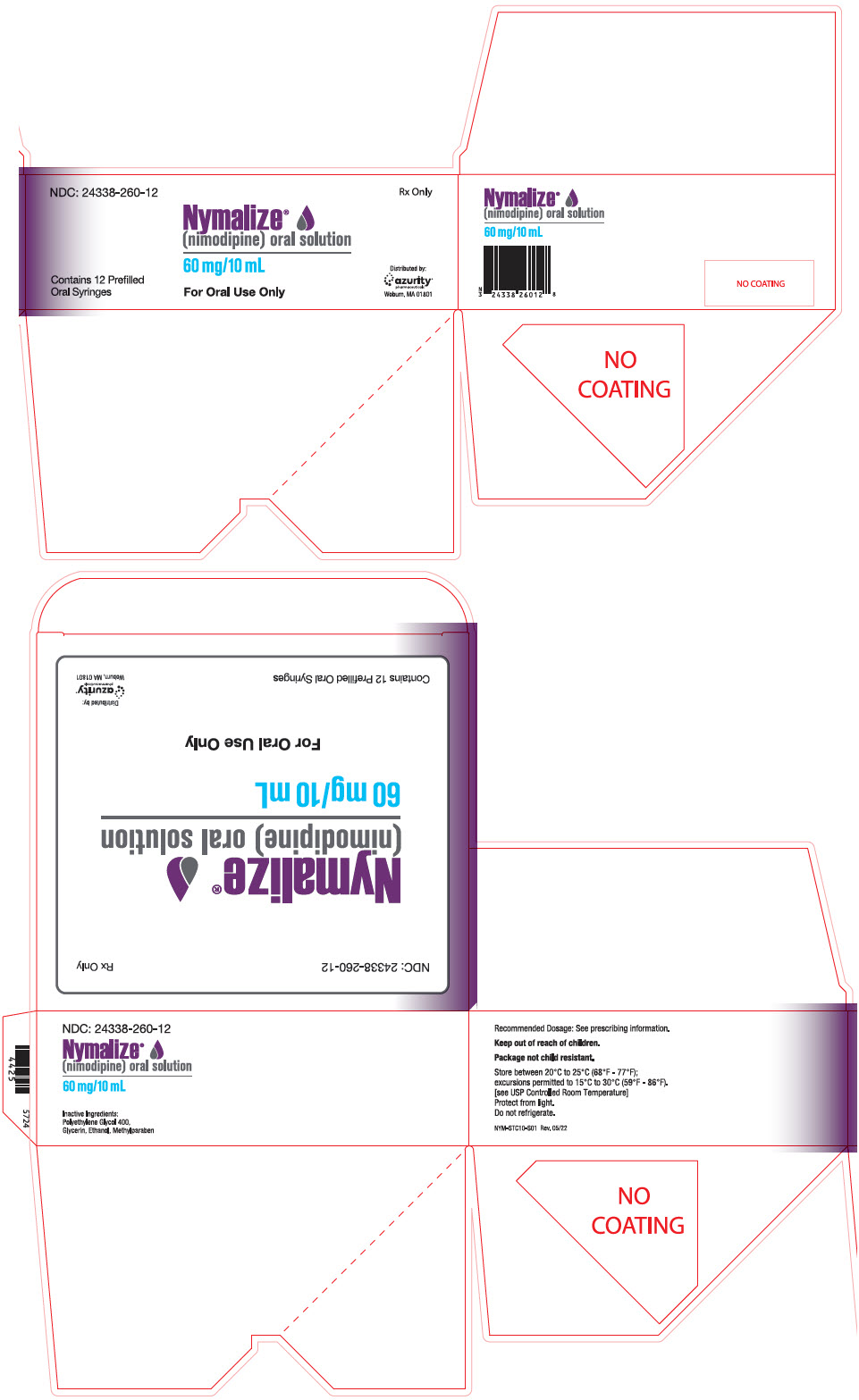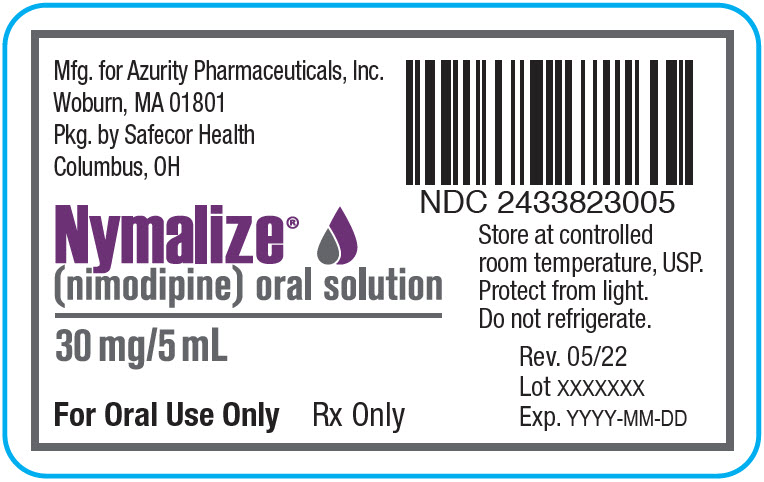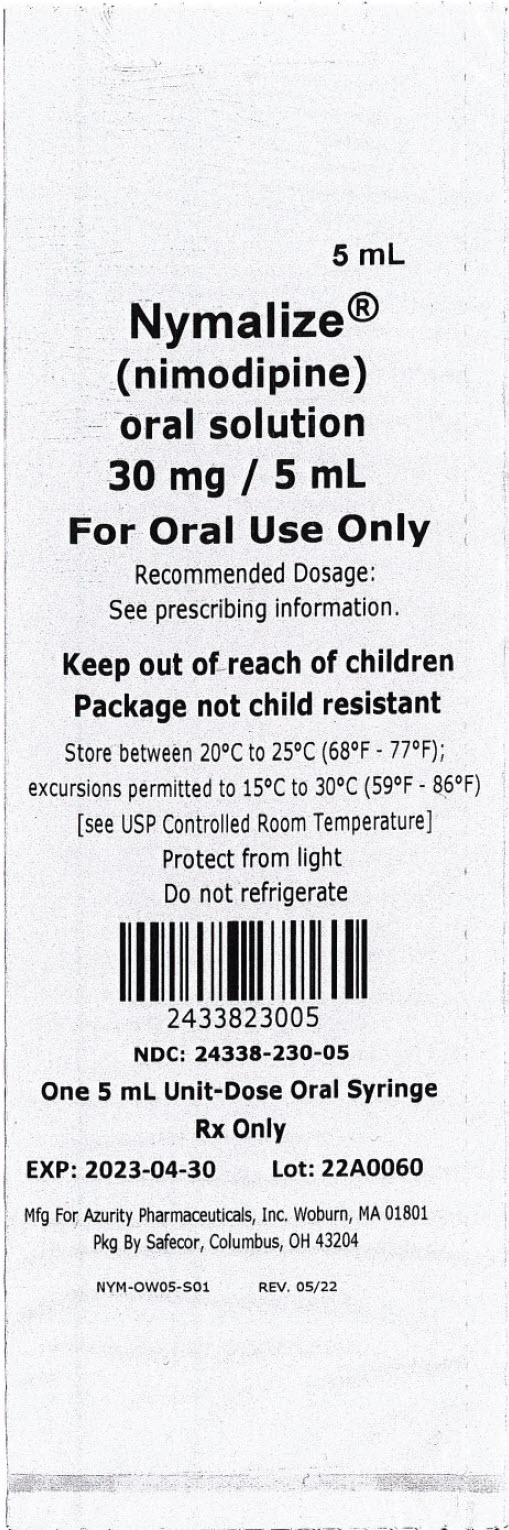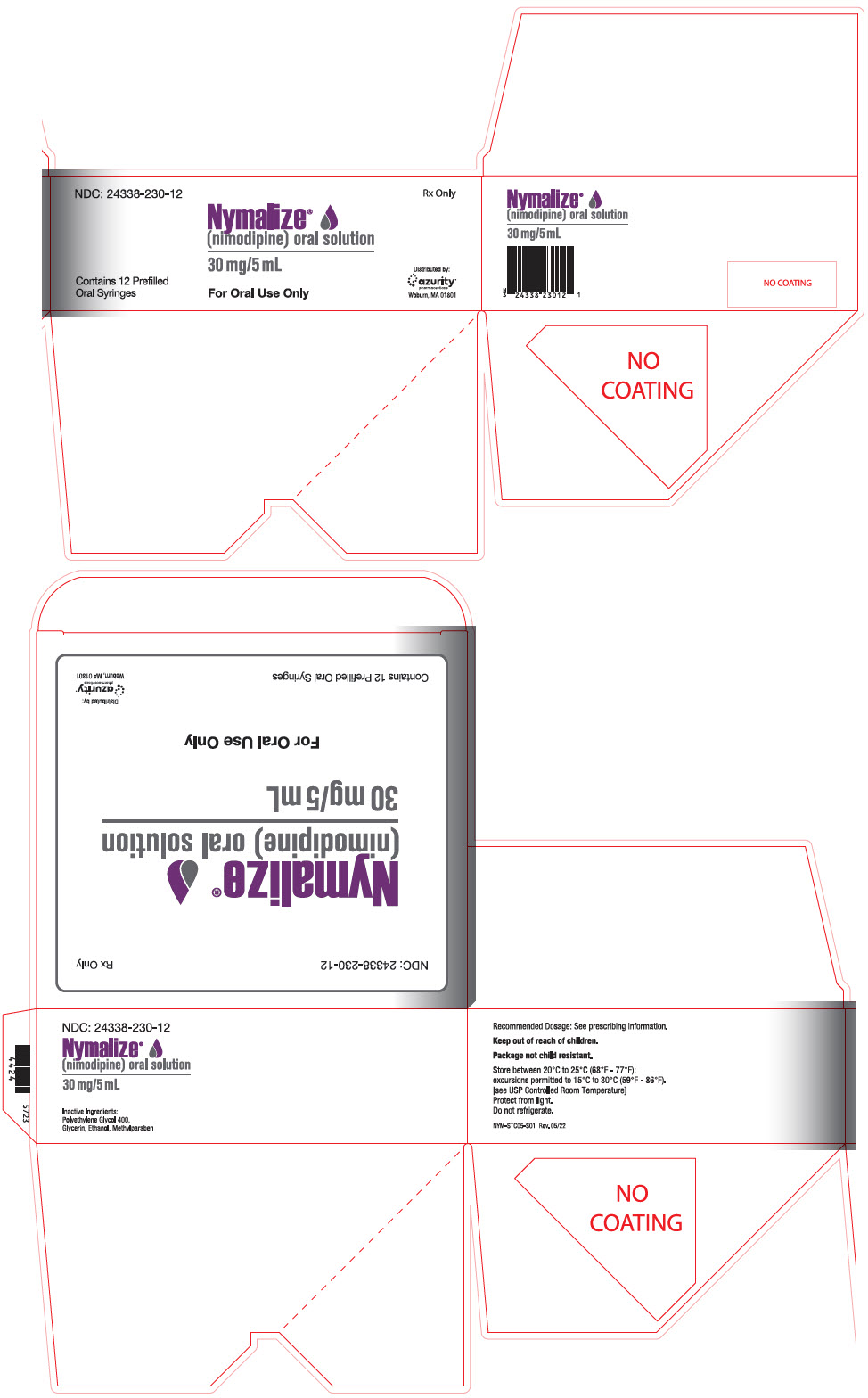 DRUG LABEL: Nymalize
NDC: 24338-260 | Form: SOLUTION
Manufacturer: Azurity Pharmaceuticals, Inc.
Category: prescription | Type: HUMAN PRESCRIPTION DRUG LABEL
Date: 20240830

ACTIVE INGREDIENTS: NIMODIPINE 60 mg/10 mL
INACTIVE INGREDIENTS: POLYETHYLENE GLYCOL 400; GLYCERIN; ALCOHOL; METHYLPARABEN

HIGHLIGHTS OF PRESCRIBING INFORMATION

These highlights do not include all the information needed to use NYMALIZE®safely and effectively. See full prescribing information for NYMALIZE.
NYMALIZE (nimodipine) oral solution
Initial U.S. Approval: 1988

1 INDICATIONS AND USAGE

NYMALIZE is a dihydropyridine calcium channel blocker indicated for the improvement of neurological outcome by reducing the incidence and severity of ischemic deficits in adult patients with subarachnoid hemorrhage (SAH) from ruptured intracranial berry aneurysms regardless of their post-ictus neurological condition (i.e., Hunt and Hess Grades I-V). (1)

2 DOSAGE AND ADMINISTRATION

- Administer only enterally (e.g., oral, nasogastric tube, or gastric tube route). Do not administer intravenously or by other parenteral routes. (2.1)
- Give one hour before a meal ortwo hours after a meal. (2.1)
- Start dosing within 96 hours of the SAH. (2.1)
- Recommended dose is 10 mL (60 mg) every 4 hours for 21 consecutive days. (2.2)
- Nasogastric or Gastric Tube Administration:Administer 10 mL (60 mg) every 4 hours with supplied prefilled oral syringe. Refill syringe with 10 mL of 0.9% saline water solution; flush remaining contents from nasogastric or gastric tube into stomach. (2.3)
- Patients with Cirrhosis:Reduce dosage to 5 mL (30 mg) every 4 hours. (2.4)

3 DOSAGE FORMS AND STRENGTHS

Oral solution (6 mg per mL):

- 60 mg per 10 mL in unit-dose prefilled syringe (3)
- 30 mg per 5 mL in unit-dose prefilled syringe (3)
- 30 mg per 5 mL in unit-dose prefilled ENFit® syringe (3)
- 60 mg per 10 mL (6 mg/mL) in 8 oz bottle (3)

4 CONTRAINDICATIONS

None (4)

5 WARNINGS AND PRECAUTIONS

- Hypotension:Monitor blood pressure. (5.1)
- Patients with Cirrhosis:Higher risk of adverse reactions. Monitor blood pressure and pulse. (5.2)
- CYP3A4 Strong Inhibitors:May significantly increase risk of hypotension. Concomitant use with NYMALIZE should generally be avoided. (5.3)
- CYP3A4 Strong Inducers:May significantly reduce efficacy of nimodipine. Concomitant use with NYMALIZE should generally be avoided. (5.4)

6 ADVERSE REACTIONS

Most common adverse reactions (incidence ≥1% and ≥1% placebo) were hypotension, headache, nausea, and bradycardia. (6.1)

To report SUSPECTED ADVERSE REACTIONS, contact Azurity Pharmaceuticals, Inc. at 1-800-461-7449 or FDA at 1-800-FDA-1088 or www.fda.gov/medwatch.

7 DRUG INTERACTIONS

- Anti-Hypertensives: May increase risk of hypotension. Monitor blood pressure. (7.1)
- CYP3A4 Moderate and Weak Inhibitors:May increase risk of hypotension. Monitor blood pressure. Dose reduction of NYMALIZE may be needed. Avoid grapefruit juice. (7.2)
- CYP3A4 Moderate and Weak Inducers:May reduce efficacy of NYMALIZE. Dose increase may be needed. (7.3)

8 USE IN SPECIFIC POPULATIONS

- Pregnancy:Based on animal data may cause fetal harm. (8.1)

FULL PRESCRIBING INFORMATION

1 INDICATIONS AND USAGE

NYMALIZE is indicated for the improvement of neurological outcome by reducing the incidence and severity of ischemic deficits in adult patients with subarachnoid hemorrhage (SAH) from ruptured intracranial berry aneurysms regardless of their post-ictus neurological condition (i.e., Hunt and Hess Grades I-V).

2 DOSAGE AND ADMINISTRATION

2.1 Administration Instructions

Administer only enterally (e.g., oral, nasogastric tube, or gastric tube route). Do not administer intravenously or by other parenteral routes. For all routes of administration, begin NYMALIZE within 96 hours of the onset of SAH. Administer one hour before a meal or two hours after a meal for all routes of administration [see Clinical Pharmacology (12.3)] .

2.2 Administration by Oral Route

The recommended oral dosage is 10 mL (60 mg) every 4 hours for 21 consecutive days.

2.3 Administration Via Nasogastric or Gastric Tube

Using the supplied prefilled oral syringe labeled "For Oral Use Only", administer 10 mL (60 mg) every 4 hours into a nasogastric or gastric tube for 21 consecutive days. For each dose, refill the syringe with 10 mL of 0.9% saline solution and then flush any remaining contents from nasogastric or gastric tube into the stomach.

2.4 Dosage Adjustments in Patients with Cirrhosis

In patients with cirrhosis, reduce the dosage to 5 mL (30 mg) every 4 hours [s ee Warnings and Precautions (5.2), Clinical Pharmacology (12.3)] .

3 DOSAGE FORMS AND STRENGTHS

Oral Solution (6 mg per mL):

- 60 mg per 10 mL, pale yellow solution in unit-dose prefilled syringe
- 30 mg per 5 mL, pale yellow solution in unit-dose prefilled syringe
- 30 mg per 5 mL, pale yellow solution in unit-dose prefilled ENFit® syringe
- 60 mg per 10 mL (6 mg/mL), pale yellow solution in 8 oz bottle

4 CONTRAINDICATIONS

None.

5 WARNINGS AND PRECAUTIONS

5.1 Hypotension

Blood pressure should be carefully monitored during treatment with NYMALIZE. In clinical studies of patients with subarachnoid hemorrhage, about 5% of nimodipine-treated patients compared to 1% of placebo-treated patients had hypotension and about 1% of nimodipine-treated patients left the study because of this [see Adverse Reactions (6)].

5.2 Possible Increased Risk of Adverse Reactions in Patients with Cirrhosis

Given that the plasma levels of nimodipine are increased in patients with cirrhosis, these patients are at higher risk of adverse reactions. Therefore, monitor blood pressure and pulse rate closely and administer a lower dosage [see Dosage and Administration (2.4), Clinical Pharmacology (12.3)] .

5.3 Possible Increased Risk of Hypotension with Strong CYP3A4 Inhibitors

Concomitant use of strong inhibitors of CYP3A4, such as some macrolide antibiotics (e.g., clarithromycin, telithromycin), some HIV protease inhibitors (e.g., indinavir, nelfinavir, ritonavir, saquinavir), some HCV protease inhibitors (e.g., boceprevir, telaprevir), some azole antimycotics (e.g., ketoconazole, itraconazole, posaconazole, voriconazole), conivaptan, delavirdine, and nefazodone with nimodipine should generally be avoided because of a risk of significant hypotension [see Drug Interactions (7.2)] .

5.4 Possible Reduced Efficacy with Strong CYP3A4 Inducers

Concomitant use of strong CYP3A4 inducers (e.g., carbamazepine, phenobarbital, phenytoin, rifampin, St. John's wort) and nimodipine should generally be avoided, as nimodipine plasma concentration and efficacy may be significantly reduced [see Drug Interactions (7.3)].

6 ADVERSE REACTIONS

The safety and efficacy of NYMALIZE (nimodipine oral solution) in the treatment of patients with SAH is based on adequate and well-controlled studies of nimodipine oral capsules in patients with SAH. NYMALIZE (nimodipine oral solution) has comparable bioavailability to nimodipine oral capsules.

The following clinically significant adverse reaction appears in other sections of the labeling:

- Hypotension [see Warnings and Precautions (5.1)].

6.1 Clinical Trials Experience

Because clinical trials are conducted under widely varying conditions, adverse reaction rates observed in the clinical trials of a drug cannot be directly compared to rates in the clinical trials of another drug and may not reflect the rates observed in clinical practice.

In clinical trials of nimodipine oral capsules in patients with SAH, eleven percent (92 of 823) of nimodipine-treated patients reported adverse events compared to six percent (29 of 479) of placebo-treated patients. The most common adverse event was decreased blood pressure in 4.4% of nimodipine-treated patients. The events reported with a frequency greater than 1% are displayed in Table 1 by dose.

Table 1: Adverse Events [n (%)] reported with a frequency > 1% in four clinical trials (Study 1, Study 2, Study 3, and Study 4)
 | Placebo (n=479) | Nimodipine dose every 4 hours
 | Placebo (n=479) | 0.35 mg/kg (n=82) | 30 mg (n=71) | 60 mg (n=494) | 90 mg (n=172) | 120 mg (n=4)
Decreased Blood Pressure | 6 (1.2) | 1 (1.2) | 0 | 19 (3.8) | 14 (8.1) | 2 (50.0)
Edema | 3 (0.6) | 0 | 0 | 2 (0.4) | 2 (1.2) | 0
Diarrhea | 3 (0.6) | 0 | 3 (4.2) | 0 | 3 (1.7) | 0
Rash | 3 (0.6) | 2 (2.4) | 0 | 3 (0.6) | 2 (1.2) | 0
Headache | 1 (0.2) | 0 | 1 (1.4) | 6 (1.2) | 0 | 0
Gastrointestinal Symptoms | 0 | 2 (2.4) | 0 | 0 | 2 (1.2) | 0
Nausea | 0 | 1 (1.2) | 1 (1.4) | 6 (1.2) | 1 (0.6) | 0
Dyspnea | 0 | 1 (1.2) | 0 | 0 | 0 | 0
EKG Abnormalities | 0 | 0 | 1 (1.4) | 0 | 1 (0.6) | 0
Tachycardia | 0 | 0 | 1 (1.4) | 0 | 0 | 0
Bradycardia | 0 | 0 | 0 | 5 (1.0) | 1 (0.6) | 0
Muscle Pain/Cramp | 0 | 0 | 1 (1.4) | 1 (0.2) | 1 (0.6) | 0
Acne | 0 | 0 | 1 (1.4) | 0 | 0 | 0
Depression | 0 | 0 | 1 (1.4) | 0 | 0 | 0

SAH is frequently accompanied by alterations in consciousness that may lead to an under-reporting of adverse experiences. As a calcium channel blocker, nimodipine may have the potential to exacerbate heart failure in susceptible patients or to interfere with A-V conduction, but these events were not observed in SAH trials.

7 DRUG INTERACTIONS

7.1 Blood Pressure Lowering Drugs

Nimodipine may increase the blood pressure lowering effect of concomitantly administered anti-hypertensives such as diuretics, beta-blockers, ACE inhibitors, angiotensin receptor blockers, other calcium channel blockers, α-adrenergic blockers, PDE5 inhibitors, and α-methyldopa. In Europe, nimodipine was observed to occasionally intensify the effect of antihypertensive drugs taken concomitantly by hypertensive patients; this phenomenon was not observed in North American clinical trials. Blood pressure should be carefully monitored, and dose adjustment of the blood pressure lowering drug(s) may be necessary.

7.2 CYP3A4 Inhibitors

Nimodipine plasma concentration can be significantly increased when concomitantly administered with strong CYP3A4 inhibitors. As a consequence, the blood pressure lowering effect may be increased. Therefore, the concomitant administration of NYMALIZE and strong CYP3A4 inhibitors should generally be avoided [ see Warnings and Precautions (5.3)]. Strong CYP3A4 inhibitors include some members of the following classes:

- macrolide antibiotics (e.g., clarithromycin, telithromycin),
- HIV protease inhibitors (e.g., indinavir, nelfinavir, ritonavir, saquinavir),
- HCV protease inhibitors (e.g., boceprevir, telaprevir),
- azole antimycotics (e.g., ketoconazole, itraconazole, posaconazole, voriconazole),
- conivaptan, delavirdine, nefazodone

Nimodipine plasma concentration can also be increased in the presence of moderate and weak inhibitors of CYP3A4. If nimodipine is concomitantly administered with these drugs, blood pressure should be monitored, and a reduction of the nimodipine dose may be necessary. Moderate and weak CYP3A4 inhibitors include alprozalam, ameprenavir, amiodarone, aprepitant, atazanavir, cimetidine, cyclosporine, diltiazem, erythromycin, fluconazole, fluoxetine, isoniazid, oral contraceptives, quinuprestin/dalfopristin, valproic acid, and verapamil.

A study in eight healthy volunteers has shown a 50% increase in mean peak nimodipine plasma concentrations and a 90% increase in mean area under the curve, after a one-week course of cimetidine at 1,000 mg/day and nimodipine at 90 mg/day. This effect may be mediated by the known inhibition of hepatic cytochrome P-450 (CYP) by cimetidine, which could decrease first-pass metabolism of nimodipine.

Grapefruit juice inhibits CYP3A4. Ingestion of grapefruit/grapefruit juice is not recommended while taking nimodipine.

7.3 CYP3A4 Inducers

Nimodipine plasma concentration and efficacy may be significantly reduced when concomitantly administered with strong CYP3A4 inducers. Therefore, concomitant use of NYMALIZE with strong CYP3A4 inducers (e.g., carbamazepine, phenobarbital, phenytoin, rifampin, St. John's wort) should generally be avoided [see Warnings and Precautions (5.4)] .

Moderate and weak inducers of CYP3A4 may also reduce the efficacy of nimodipine. Patients on these should be closely monitored for lack of effectiveness, and a nimodipine dosage increase may be required. Moderate and weak CYP3A4 inducers include, for example: amprenavir, aprepitant, armodafinil, bosentan, efavirnenz, etravirine, Echinacea, modafinil, nafcillin, pioglitazone, prednisone, rufinamide, and vemurafenib.

8 USE IN SPECIFIC POPULATIONS

8.1 Pregnancy

Risk Summary

There are no adequate data on the developmental risk associated with the use of NYMALIZE in pregnant women. In animal studies, oral administration of nimodipine during pregnancy resulted in adverse effects on development (increased embryofetal mortality, increased incidences of fetal structural abnormalities, decreased fetal growth) at doses equivalent to (rat) or less than (rabbit) those used clinically [see Data] .

In the U.S. general population, the estimated background risk of major birth defects and miscarriage in clinically recognized pregnancies is 2-4% and 15-20%, respectively. The background risk of major birth defects and miscarriage for the indicated population is unknown.

Data

Animal Data

Nimodipine has been shown to have a teratogenic effect in two studies in rabbit. In one study, incidences of malformations and stunted fetuses were increased at oral doses of 1 mg/kg/day and 10 mg/kg/day administered throughout organogenesis but not at 3 mg/kg/day. In the second study, an increased incidence of stunted fetuses was seen at 1 mg/kg/day but not at higher doses (3 mg/kg/day and 10 mg/kg/day). The lowest effect dose in rabbits (1 mg/kg/day) is less than the recommended human dose (RHD) of 360 mg/day on a body surface area (mg/m^2) basis.

Nimodipine was embryotoxic, causing resorption and stunted growth of fetuses in rats at 100 mg/kg/day administered orally throughout organogenesis; this dose is approximately 3 times the RHD on a mg/m^2basis. In two other studies in rats, nimodipine administered orally at 30 mg/kg/day throughout organogenesis and continued until sacrifice (day 20 of pregnancy or day 21 postpartum) was associated with higher incidences of skeletal variation, stunted fetuses, and stillbirths but no malformations; this dose is similar to the RHD on a mg/m^2basis.

8.2 Lactation

Risk Summary

Nimodipine has been detected in human milk. There are no data on the effects of nimodipine on the breastfed infant or on milk production.

The developmental and health benefits of breastfeeding should be considered along with the mother's clinical need for NYMALIZE and any potential adverse effects on the breastfed infant from NYMALIZE or from the underlying maternal condition.

Data

Animal Data

[^14C]Nimodipine and its radiolabeled metabolites were secreted in milk of orally dosed lactating rats. The milk concentration of nimodipine and/or metabolites was higher than that in plasma, with a milk/plasma ratio of 0.65 to 4.7.

8.4 Pediatric Use

Safety and effectiveness in pediatric patients have not been established.

8.5 Geriatric Use

Clinical studies of nimodipine did not include sufficient numbers of subjects aged 65 and over to determine whether they had a different clinical response than younger subjects. Other reported clinical experience has not identified differences in responses between the elderly and younger patients. In general, dosing in elderly patients should be cautious, reflecting the greater frequency of decreased hepatic, renal or cardiac function, and of concomitant disease or other drug therapy [see Clinical Pharmacology (12.3)] .

10 OVERDOSAGE

There have been no reports of overdosage from the oral administration of nimodipine. Symptoms of overdosage would be expected to be related to cardiovascular effects such as excessive peripheral vasodilation with marked systemic hypotension. Clinically significant hypotension due to nimodipine overdosage may require active cardiovascular support with pressor agents and specific treatments for calcium channel blocker overdose. Since nimodipine is highly protein-bound, dialysis is not likely to be of benefit.

11 DESCRIPTION

NYMALIZE contains nimodipine, a dihydropyridine calcium channel blocker. Nimodipine is isopropyl 2-methoxyethyl 1,4-dihydro-2,6-dimethyl-4-(m-nitrophenyl)-3,5-pyridinedicarboxylate. It has a molecular weight of 418.5 and a molecular formula of C21H26N2O7. The structural formula is:

Nimodipine is a yellow crystalline substance, practically insoluble in water.

NYMALIZE Oral Solution contains 60 mg of nimodipine per 10 mL. In addition, the oral solution contains the following inactive ingredients: ethanol, glycerin, methylparaben, polyethylene glycol 400.

12 CLINICAL PHARMACOLOGY

12.1 Mechanism of Action

Nimodipine is a dihydropyridine calcium channel blocker. The contractile processes of smooth muscle cells are dependent upon calcium ions, which enter these cells during depolarization as slow ionic transmembrane currents. Nimodipine inhibits calcium ion transfer into these cells and thus inhibits contractions of vascular smooth muscle. In animal experiments, nimodipine had a greater effect on cerebral arteries than on arteries elsewhere in the body perhaps because it is highly lipophilic, allowing it to cross the blood-brain barrier; concentrations of nimodipine as high as 12.5 ng/mL have been detected in the cerebrospinal fluid of nimodipine-treated SAH patients.

The precise mechanism of action of nimodipine in reducing the incidence and severity of ischemic deficits in adult patients with SAH from ruptured intracranial berry aneurysms is unknown. Although the clinical studies demonstrate a favorable effect of nimodipine on the severity of neurological deficits caused by cerebral vasospasm following SAH, there is no arteriographic evidence that nimodipine either prevents or relieves the spasm of these arteries. However, whether or not the arteriographic methodology utilized was adequate to detect a clinically meaningful effect, if any, on vasospasm is unknown.

12.3 Pharmacokinetics

After a single 60 mg oral dose of NYMALIZE, mean (CV%) Cmaxwas 69.9 ng/mL (36.1%), AUCinfwas 151 h ∙ng/mL (36.0%) and within subject variability (CV%) was 21.7% and 12.4%, respectively. There were no signs of accumulation when nimodipine was given three times a day for seven days.

Absorption

In humans, nimodipine was absorbed with a time to maximum concentration (Tmax) ranging from 0.25 to 1.05 hours following oral administration. Because of a high first-pass metabolism, the bioavailability of nimodipine averages 13% after oral administration.

Effect of Food

In a study of 24 healthy male volunteers, administration of nimodipine capsules following a standard breakfast resulted in a 68% lower peak plasma concentration and 38% lower bioavailability relative to dosing under fasted conditions [see Dosage and Administration (2.1)] .

Distribution

Nimodipine is over 95% bound to plasma proteins. The binding was concentration independent over the range of 10 ng/mL to 10 mcg/mL.

Elimination

The terminal elimination half-life is approximately 8 to 9 hours but earlier elimination rates are much more rapid, equivalent to a half-life of 1-2 hours; a consequence is the need for frequent (every 4 hours) dosing.

Metabolism

Numerous metabolites, all of which are either inactive or considerably less active than the parent compound, have been identified. The metabolism of nimodipine is mediated by CYP3A4 [see Drug Interactions (7.2, 7.3)].

Excretion

Nimodipine is eliminated almost exclusively in the form of metabolites and less than 1% is recovered in the urine as unchanged drug.

Specific Populations

Patients with Cirrhosis

The bioavailability of nimodipine is significantly increased in patients with cirrhosis, with Cmaxapproximately double that in normals, which necessitates lowering the dose in this group of patients [see Dosage and Administration (2.4), Warnings and Precautions (5.2)] .

Geriatric Patients

In a single parallel-group study involving 24 elderly subjects (aged 59-79 years) and 24 younger subjects (aged 22-40 years), the observed AUC and Cmaxof nimodipine was approximately 2-fold higher in the elderly population compared to the younger study subjects following oral administration (given as a single dose of 30 mg and dosed to steady-state with 30 mg three times daily [less than the recommended dosing regimen] for 6 days). The clinical response to these age-related pharmacokinetic differences, however, was not considered significant [see Use in Specific Populations (8.5)].

13 NONCLINICAL TOXICOLOGY

13.1 Carcinogenesis, Mutagenesis, Impairment of Fertility

Carcinogenesis

In a two-year study in rats, the incidences of adenocarcinoma of the uterus and Leydig cell adenoma of the testes were increased at 1800 ppm nimodipine in the diet (approximately 90-120 mg/kg/day). The increases were not statistically significant, however, and the higher rates were within the historical control range for these tumors. Nimodipine was found not to be carcinogenic in a 91-week mouse study, but the high dose of 1800 ppm nimodipine in the diet (approximately 550-775 mg/kg/day) was associated with an increased mortality rate.

Mutagenesis

Mutagenicity studies, including the Ames, micronucleus, and dominant lethal assays, were negative.

Impairment of Fertility

Nimodipine did not impair the fertility and general reproductive performance of male and female rats following oral doses of up to 30 mg/kg/day when administered prior to mating and continuing in females to day 7 of pregnancy. This dose in a rat is similar to a clinical dose of 60 mg every 4 hours in a 60 kg patient, on a body surface area (mg/m^2) basis.

14 CLINICAL STUDIES

The safety and efficacy of NYMALIZE (nimodipine oral solution) in the treatment of patients with SAH is based on adequate and well-controlled studies of nimodipine oral capsules in patients with SAH. NYMALIZE (nimodipine oral solution) has comparable bioavailability to nimodipine oral capsules.

Nimodipine has been shown in 4 randomized, double-blind, placebo-controlled trials to reduce the severity of neurological deficits resulting from vasospasm in patients who have had a recent SAH (Studies 1, 2, 3, and 4).

The trials used doses ranging from 20-30 mg to 90 mg every 4 hours, with drug given for 21 days in 3 studies, and for at least 18 days in the other. Three of the four trials followed patients for 3-6 months. Three of the trials studied relatively well patients, with all or most patients in Hunt and Hess Grades I - III (essentially free of focal deficits after the initial bleed). Study 4 studied much sicker patients with Hunt and Hess Grades III - V. Studies 1 and 2 were similar in design, with relatively unimpaired SAH patients randomized to nimodipine or placebo. In each, a judgment was made as to whether any late-developing deficit was due to spasm or other causes, and the deficits were graded. Both studies showed significantly fewer severe deficits due to spasm in the nimodipine group; Study 2 showed fewer spasm-related deficits of all severities. No effect was seen on deficits not related to spasm. See Table 2.

Table 2: Deficits in Patients with Hunt and Hess Grades I to III in Study 1 and Study 2
Study | Grade [Hunt and Hess Grade] | Treatment | Patients
Study | Grade [Hunt and Hess Grade] | Treatment | Number Analyzed | Number of Patients with Any Deficit Due to Spasm | Numbers with Severe Deficit
Study 1 | I-III | Nimodipine 20-30 mg every 4 hours | 56 | 13 | 1
Study 1 | I-III | Placebo | 60 | 16 | 8 [p=0.03]
Study 2 | I-III | Nimodipine 60 mg every 4 hours | 31 | 4 | 2
Study 2 | I-III | Placebo | 39 | 11 | 10

Study 3 was a 554-patient trial that included SAH patients with all grades of severity (89% were in Hunt and Hess Grades I-III). In Study 3, patients were treated with placebo or 60 mg of nimodipine every 4 hours. Outcomes were not defined as spasm related or not but there was a significant reduction in the overall rate of brain infarction and severely disabling neurological outcome at 3 months (Table 3):

Table 3: Degree of Recovery or Disability in Study 3 (89% Hunt and Hess Grades I-III)
 | Nimodipine | Placebo
Total patients | 278 | 276
Good recovery | 199 [p = 0.0444 – good and moderate vs severe and dead] | 169
Moderate disability | 24 | 16
Severe disability | 12 [p = 0.001 – severe disability] | 31
Death | 43 [p = 0.056 – death] | 60

Study 4 enrolled much sicker patients, (Hunt and Hess Grades III-V), who had a high rate of death and disability, and used a dose of 90 mg every 4 hours, but was otherwise similar to Study 1 and Study 2. Analysis of delayed ischemic deficits, many of which result from spasm, showed a significant reduction in spasm-related deficits. Among analyzed patients (72 nimodipine, 82 placebo), there were the following outcomes (Table 4).

Table 4: Neurological Ischemic Deficits in Study 4 [Hunt and Hess Grades III-V]
 | Delayed Ischemic Deficits (DID) |  | Permanent Deficits
 | Nimodipine 90 mg every 4 hours | Placebo | Nimodipine 90 mg every 4 hours | Placebo
 | n (%) | n (%) | n (%) | n (%)
DID Spasm Alone | 8 (11) [p = 0.001, Nimodipine vs placebo] | 25 (31) | 5 (7) | 22 (27)
DID Spasm Contributing | 18 (25) | 21 (26) | 16 (22) | 17 (21)
DID Without Spasm | 7 (10) | 8 (10) | 6 (8) | 7 (9)
No DID | 39 (54) | 28 (34) | 45 (63) | 36 (44)

When data were combined for Study 3 and Study 4, the treatment difference on success rate (i.e., good recovery) on the Glasgow Outcome Scale was 25.3% (nimodipine) versus 10.9% (placebo) for Hunt and Hess Grades IV or V. Table 5 demonstrates that nimodipine tends to improve good recovery of SAH patients with poor neurological status post-ictus, while decreasing the numbers with severe disability and vegetative survival.

Table 5: Glasgow Outcome Scale in Combined Studies 3 and 4
Glasgow Outcome [p = 0.045, nimodipine vs. placebo] | Nimodipine (n=87) | Placebo (n=101)
Good Recovery | 22 (25.3%) | 11 (10.9%)
Moderate Disability | 8 (9.2%) | 12 (11.9%)
Severe Disability | 6 (6.9%) | 15 (14.9%)
Vegetative Survival | 4 (4.6%) | 9 (8.9%)
Death | 47 (54.0%) | 54 (53.5%)

A dose-ranging study comparing 30 mg, 60 mg, and 90 mg doses found a generally low rate of spasm-related neurological deficits but no dose response relationship.

16 HOW SUPPLIED/STORAGE AND HANDLING

NYMALIZE (nimodipine) Oral Solution 6 mg/mL is a pale yellow solution and is supplied as follows:

- NDC 24338-260-08: 8 oz. bottle (237 mL) 60 mg/10 mL (6 mg/mL)
- NDC 24338-260-12: Carton containing 12 individually wrapped 10 mL packages.
  Each package contains one 60 mg/10 mL unit-dose prefilled oral syringe with a purple plunger (NDC 24338-260-10).
- NDC 24338-230-12: Carton containing 12 individually wrapped 5 mL packages.
  Each package contains one 30 mg/5 mL unit-dose prefilled oral syringe with a white plunger (NDC 24338-230-05).
- NDC 24338-230-30: Carton containing 12 blisters.
  Each blister contains one 30 mg/5 mL unit-dose prefilled ENFit®oral syringe (NDC 24338-230-15).

STORAGE AND HANDLING

Store between 20ºC to 25ºC (68ºF to 77ºF); excursions permitted to 15ºC to 30ºC (59ºF to 86ºF) [see USP Controlled Room Temperature].

Protect from light.

Do not refrigerate.

17 PATIENT COUNSELING INFORMATION

Inform patients that the most frequent adverse reaction associated with nimodipine is decreased blood pressure [ see Warnings and Precautions (5.1)] .Inform them that use of NYMALIZE with anti-hypertensives can cause increased drop in blood pressure [see Drug Interactions (7.1)] .

Patients should be aware that ingestion of grapefruit or grapefruit juice should be avoided when taking NYMALIZE due to its ability to increase nimodipine plasma concentrations and potential to increase the risk of hypotension [see Drug Interactions (7.2)] .

Advise patients to notify their healthcare provider if they become pregnant during treatment or plan to become pregnant during therapy [see Use in Specific Populations (8.1)] .

Advise female patients to notify their physicians if they intend to breastfeed or are breastfeeding an infant [see Use in Specific Populations (8.2)] .

Manufactured for:
Azurity Pharmaceuticals, Inc.
Woburn, MA 01801

Manufactured by:
Delpharm Montréal Inc.
Pointe-Claire, QC, Canada
H9R 1B4

Patent: https://azurity.com/patents_and_trademarks/

This product's labeling may have been updated. For current Full Prescribing Information, please visit www.nymalize.com.

Manufactured for: Azurity Pharmaceuticals, Inc. Woburn, MA 01801

NYMALIZE is a registered trademark of Azurity Pharmaceuticals, Inc.

NIM-PI-12 Rev. AUG2024

PRINCIPAL DISPLAY PANEL - 10 mL Syringe Label

Mfg. for Azurity Pharmaceuticals, Inc.
Woburn, MA 01801
Pkg. by Safecor Health
Columbus, OH

NDC 2433826010

Store at controlled
room temperature, USP.
Protect from light.
Do not refrigerate.

Nymalize®
(nimodipine) oral solution

60 mg/10 mL

For Oral Use Only
Rx Only

Rev. 05/22
Lot XXXXXXX
Exp. YYYY-MM-DD

PRINCIPAL DISPLAY PANEL - 10 mL Syringe Package

10 mL

Nymalize®
(nimodipine)
oral solution

60 mg / 10 mL

For Oral Use Only

Recommended Dosage:
See prescribing information.

Keep out of reach of children
Package not child resistant

Store between 20°C to 25°C (68°F - 77°F);
excursions permitted to 15°C to 30°C (59°F - 86°F)
[see USP Controlled Room Temperature]
Protect from light
Do not refrigerate

NDC: 24338-260-10

One 10 mL Unit-Dose Oral Syringe

Rx Only

EXP: 2023-05-31
Lot: 22A0047

Mfg For Azurity Pharmaceuticals, Inc. Woburn, MA 01801
Pkg By Safecor, Columbus, OH 43204

NYM-OW10-S01
REV. 05/22

PRINCIPAL DISPLAY PANEL - 10 mL Syringe Package Carton

NDC: 24338-260-12
Rx Only

Nymalize®
(nimodipine) oral solution

60 mg/10 mL

Contains 12 Prefilled
Oral Syringes

For Oral Use Only

Distributed by:
azurity®
pharmaceuticals
Woburn, MA 01801

PRINCIPAL DISPLAY PANEL - 5 mL Syringe Label

Mfg. for Azurity Pharmaceuticals, Inc.
Woburn, MA 01801
Pkg. by Safecor Health
Columbus, OH

NDC 2433823005

Store at controlled
room temperature, USP.
Protect from light.
Do not refrigerate.

Nymalize®
(nimodipine) oral solution

30 mg/5 mL

For Oral Use Only
Rx Only

Rev. 05/22
Lot XXXXXXX
Exp. YYYY-MM-DD

PRINCIPAL DISPLAY PANEL - 5 mL Syringe Package

5 mL

Nymalize®
(nimodipine)
oral solution

30 mg / 5 mL

For Oral Use Only

Recommended Dosage:
See prescribing information.

Keep out of reach of children
Package not child resistant

Store between 20°C to 25°C (68°F - 77°F);
excursions permitted to 15°C to 30°C (59°F - 86°F)
[see USP Controlled Room Temperature]
Protect from light
Do not refrigerate

NDC: 24338-230-05

One 5 mL Unit-Dose Oral Syringe

Rx Only

EXP: 2023-04-30
Lot: 22A0060

Mfg For Azurity Pharmaceuticals, Inc. Woburn, MA 01801
Pkg By Safecor, Columbus, OH 43204

NYM-OW05-S01
REV. 05/22

PRINCIPAL DISPLAY PANEL - 5 mL Syringe Package Carton

NDC: 24338-230-12
Rx Only

Nymalize®
(nimodipine) oral solution

30 mg/5 mL

Contains 12 Prefilled
Oral Syringes

For Oral Use Only

Distributed by:
azurity®
pharmaceuticals
Woburn, MA 01801

PRINCIPAL DISPLAY PANEL - 5 mL ENFit® Syringe Label

NDC 24338-230-15

Rx Only

Nymalize®
(nimodipine) oral solution

30 mg/5 mL

ENFit®Syringe

For Oral Use Only

PRINCIPAL DISPLAY PANEL - 5 mL ENFit® Syringe Blister Label

NDC 24338-230-15

Rx Only

Nymalize®
(nimodipine) oral solution

30 mg/5 mL ENFit®Syringe

One 5 mL ENFit®Syringe

For Oral Use Only

Store between 20°C to 25°C (68°F - 77°F); excursions permitted to 15°C to 30°C (59°F- 86°F).
[see USP Controlled Room Temperature] Protect from light. Do not refrigerate.

Manufactured for:

azurity®Pharmaceuticals

Woburn, MA 01801

PRINCIPAL DISPLAY PANEL - 5 mL ENFit® Syringe Carton Label

NDC 24338-230-30

Rx Only

Nymalize®
(nimodipine) oral solution

30 mg/5 mL ENFit® Syringe

Contains 12 Prefilled ENFit® Oral Syringes

For Oral Use Only

Recommended Dosage: See prescribing information.

Keep out of reach of children.

Package not child resistant.

Store between 20°C to 25°C (68°F - 77°F); excursions permitted to 15°C to 30°C (59°F- 86°F).
[see USP Controlled Room Temperature] Protect from light. Do not refrigerate.

Manufactured for:

azurity® Pharmaceuticals

Woburn, MA 01801